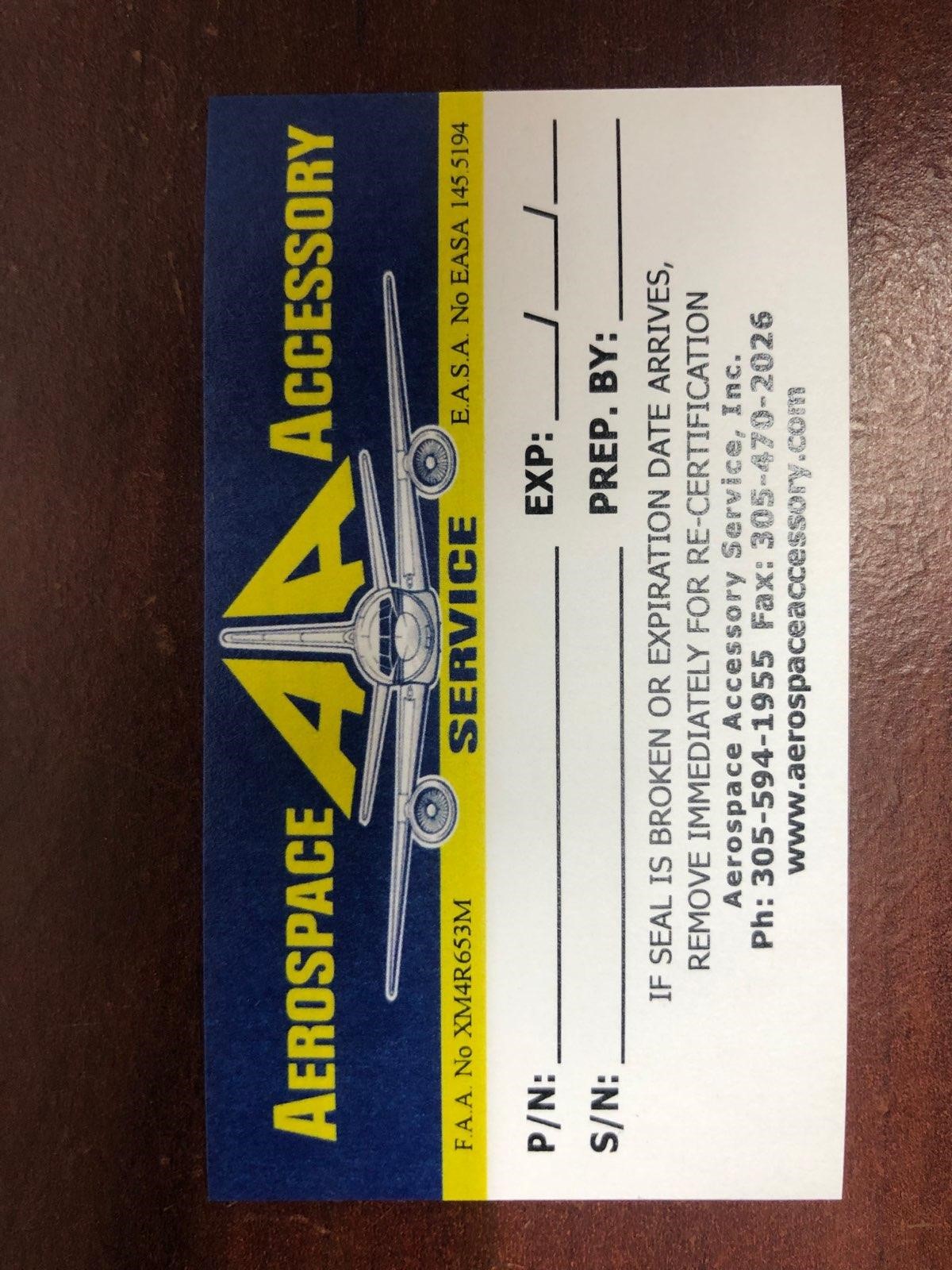 DRUG LABEL: Model AA 2012
NDC: 27860-002 | Form: KIT | Route: TOPICAL
Manufacturer: Aerospace Accessory Service, Inc
Category: other | Type: MEDICAL DEVICE
Date: 20210505

ACTIVE INGREDIENTS: BENZALKONIUM CHLORIDE 0.13 g/100 g; BENZALKONIUM CHLORIDE 1.3 mg/1 mL
INACTIVE INGREDIENTS: WATER; WATER

Model AA 2012

Aerospace Accessory Service

P/N:

S/N:

EXP:

Prep. By: